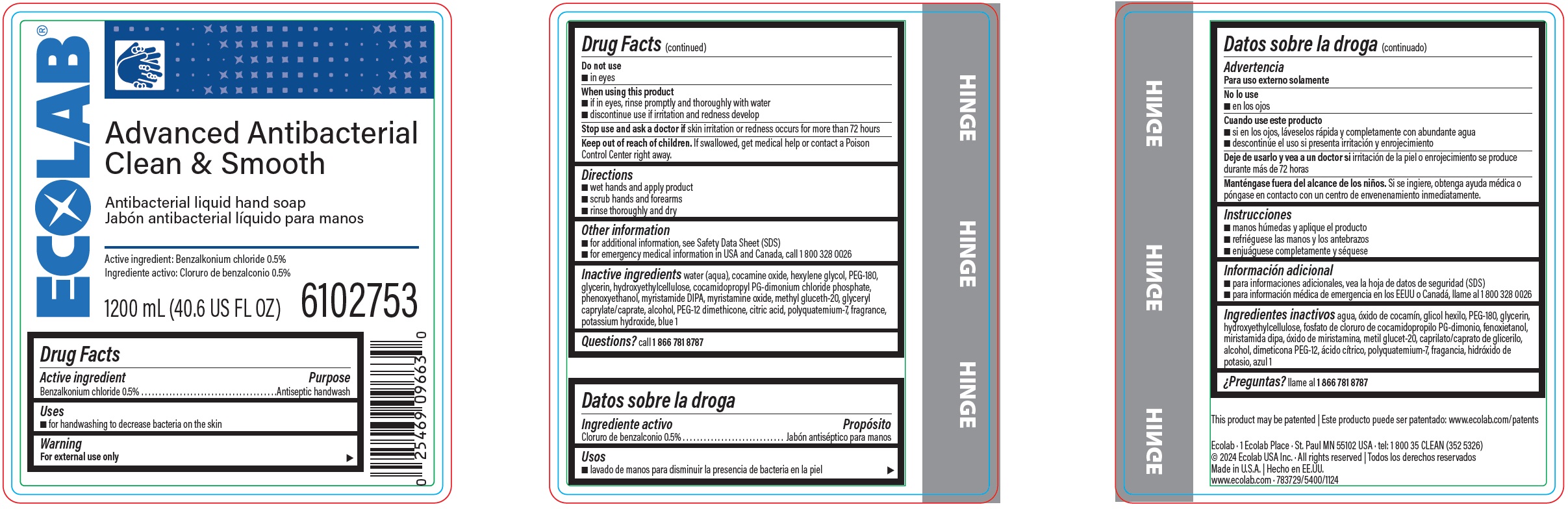 DRUG LABEL: Advanced Antibacterial Clean and Smooth
NDC: 47593-575 | Form: SOLUTION
Manufacturer: Ecolab Inc.
Category: otc | Type: HUMAN OTC DRUG LABEL
Date: 20241210

ACTIVE INGREDIENTS: BENZALKONIUM CHLORIDE 5 mg/1 mL
INACTIVE INGREDIENTS: WATER; COCAMINE OXIDE; HEXYLENE GLYCOL; POLYETHYLENE GLYCOL 8000; GLYCERIN; HYDROXYETHYL CELLULOSE (4000 MPA.S AT 1%); COCAMIDOPROPYL PG-DIMONIUM CHLORIDE PHOSPHATE; PHENOXYETHANOL; MYRISTIC DIISOPROPANOLAMIDE; MYRISTAMINE OXIDE; METHYL GLUCETH-20; GLYCERYL CAPRYLATE/CAPRATE; ALCOHOL; PEG-12 DIMETHICONE; ANHYDROUS CITRIC ACID; POLYQUATERNIUM-7 (70/30 ACRYLAMIDE/DADMAC; 1600000 MW); POTASSIUM HYDROXIDE; FD&C BLUE NO. 1

Drug Facts

Active ingredient

Benzalkonium Chloride, 0.5%

Purpose

Antiseptic handwash

Uses

for handwashing to decrease bacteria on the skin

Warnings

For external use only

Do not use

- in eyes

When using the product

- if in eyes, rinse promptly and thoroughly with water
- discontinue use if irritation and redness develop

Stop use and ask a doctor if

- skin irritation or redness occurs for more than 72 hours

Keep out of reach of children. If swallowed, get medical help or contact a Poison Control Center right away.

Directions

- wet hands and apply product
- scrub hands and forearms
- rinse thoroughly and dry

Other information

- for additional information, see Safety Data Sheet (SDS)
- for emergency medical information in USA and Canada, call 1 800 328 0026

INACTIVE INGREDIENT

Inactive ingredients water (aqua), cocamine oxide, hexylene glycol, PEG-180, glycerin, hydroxyethylcellulose, cocamidopropyl PG-dimonium chloride phosphate, phenoxyethanol, myristamide DIPA, myristamine oxide, methyl gluceth-20, glyceryl caprylate/caprate, alcohol, PEG-12 dimethicone, citric acid, polyquaternium-7, fragrance, potassium hydroxide, blue 1

Questions? call 1-866-781-8787

Representative label & Primary display panel

ECOLAB

Advanced Antibacterial

Clean & Smooth

Antibacterial liquid hand soap

Active Ingredient: Benzalkonium chloride 0.5%

1200 mL (40.6 US FL OZ) 6102753

Ecolab · 1 Ecolab Place · St. Paul MN 55102 USA · tel: 1 800 35 CLEAN (352 5326)

© 2024 Ecolab USA Inc. · All rights reserved | Todos los derechos reservados

Made in U.S.A. | Hecho en EE.UU.

www.ecolab.com 783729/5400/1124